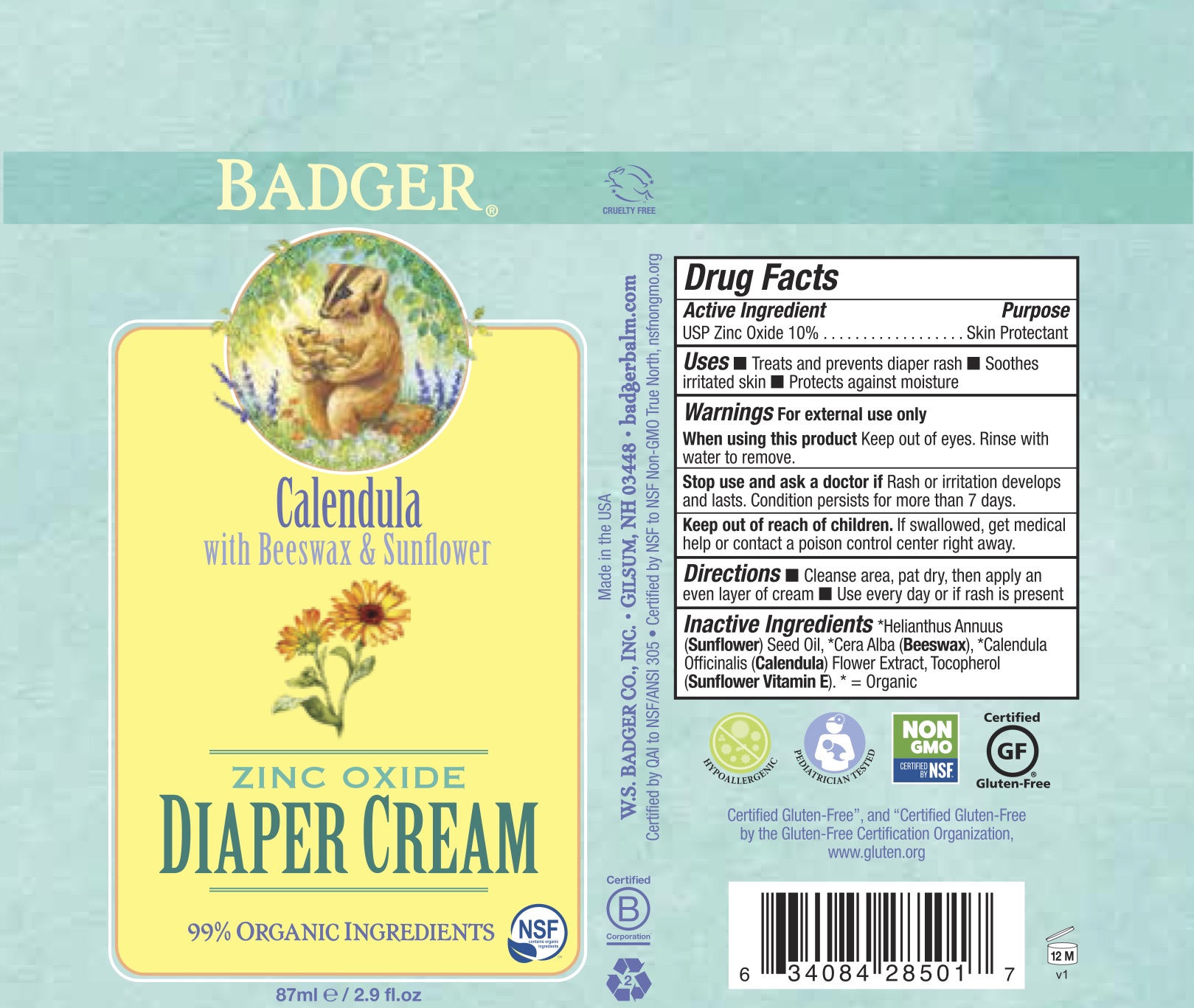 DRUG LABEL: Badger Diaper
NDC: 62206-2850 | Form: CREAM
Manufacturer: W.S. Badger Company, Inc.
Category: otc | Type: HUMAN OTC DRUG LABEL
Date: 20241231

ACTIVE INGREDIENTS: ZINC OXIDE 10 g/100 mL
INACTIVE INGREDIENTS: SUNFLOWER OIL; YELLOW WAX; TOCOPHEROL; HIPPOPHAE RHAMNOIDES FRUIT; CALENDULA OFFICINALIS FLOWER

Badger®Diaper Cream

Drug Facts

Active Ingredient

USP Zinc Oxide 10%

Purpose

Skin Protectant

Uses

- Treats and prevents diaper rash
- Soothes irritated skin
- Protects against moisture

Warnings

For external use only

When using this product

Keep out of eyes. Rinse with water to remove.

Stop use and ask a doctor if

Rash or irritation develops and lasts. Condition persists for more than 7 days.

Keep out of reach of children.If swallowed, get medical help or contact a poison control center right away.

Directions

- Cleanse area, pat dry, then apply an even layer of cream
- Use every day or if rash is present

Ingredients

[= Certified Organic] Helianthus Annuus (Sunflower) Oil, Cera Alba (Beeswax), Calendula Officinalis (Calendula) CO2Extract, Tocopherol (Sunflower Vitamin E).

PRINCIPAL DISPLAY PANEL - 87 ml Tube Label

BADGER®

Calendula
with Beeswax & Sunflower

ZINC OXIDE
DIAPER CREAM

99% ORGANIC INGREDIENTS

NSF
contains organic
ingredients

87ml/2.9 fl.oz